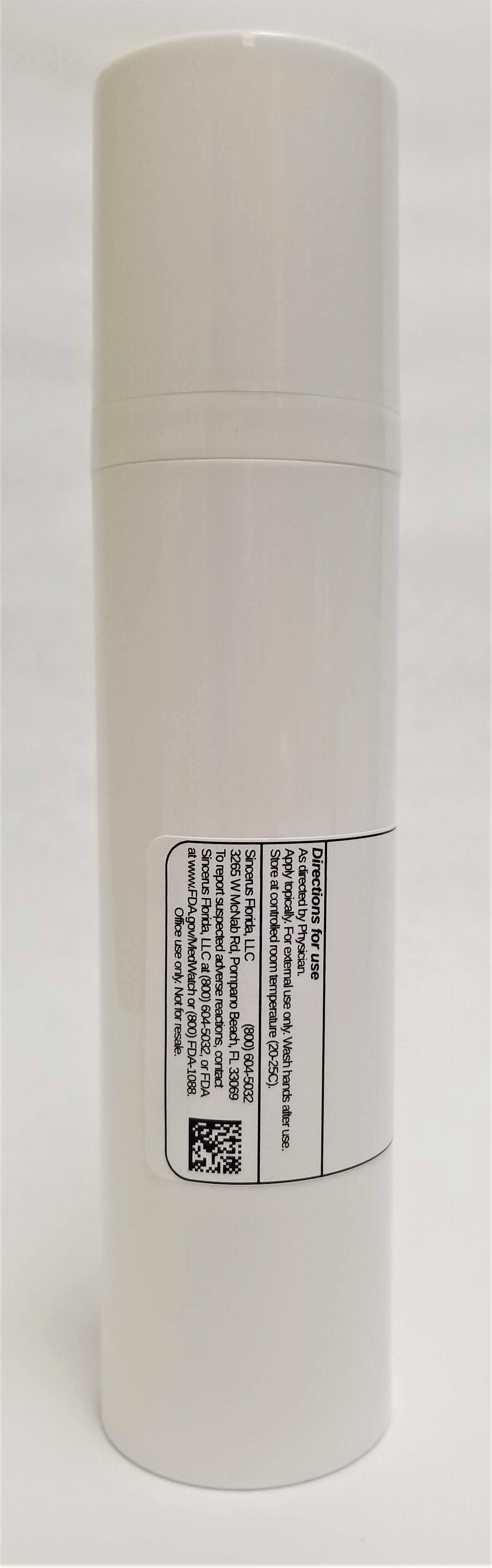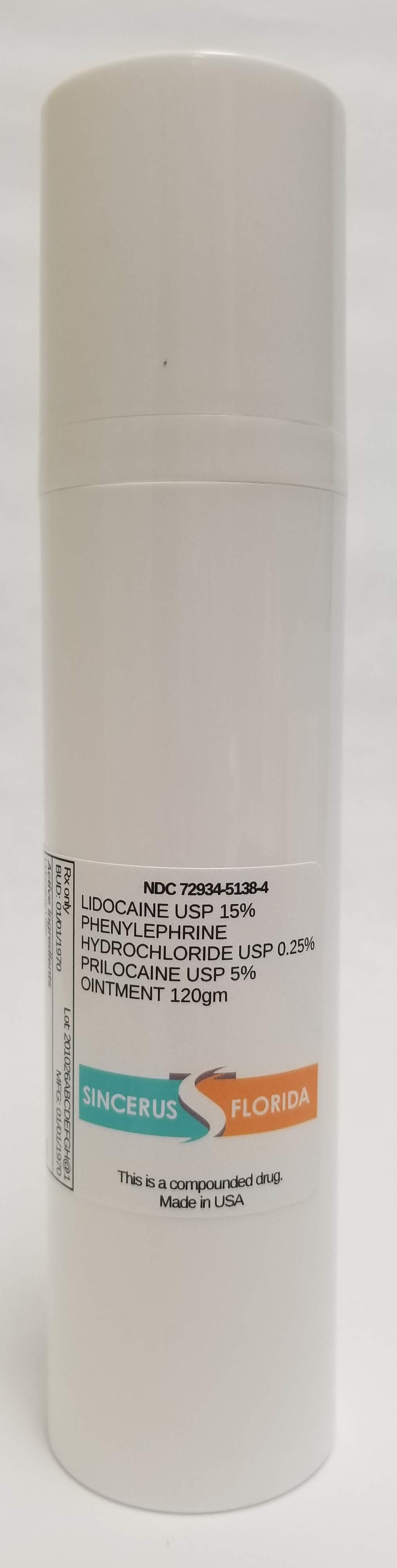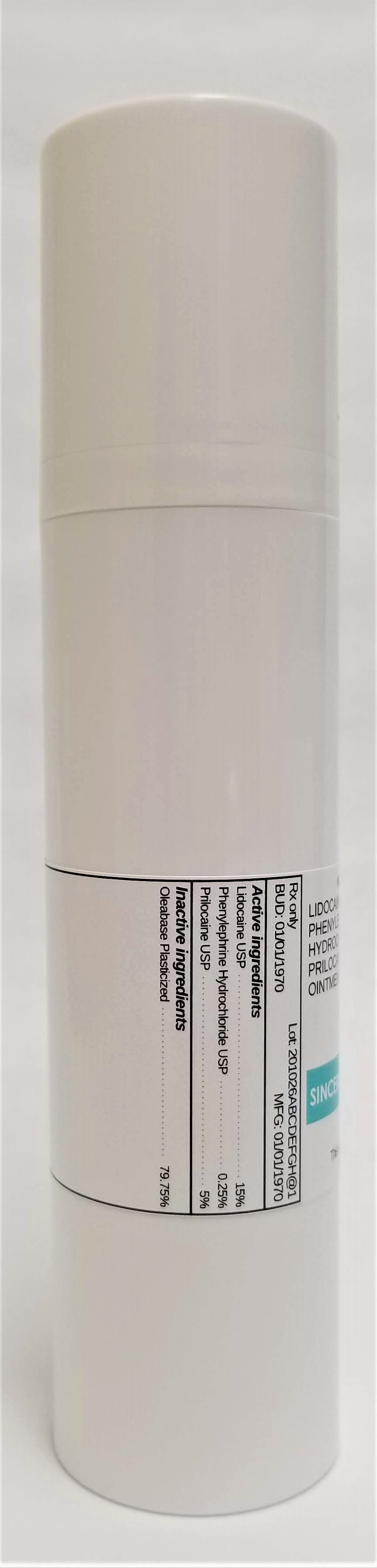 DRUG LABEL: LIDOCAINE 15% / PHENYLEPHRINE HCL 0.25% / PRILOCAINE 5%
NDC: 72934-5138 | Form: OINTMENT
Manufacturer: Sincerus Florida, LLC
Category: prescription | Type: HUMAN PRESCRIPTION DRUG LABEL
Date: 20190516

ACTIVE INGREDIENTS: LIDOCAINE 15 g/100 g

LIDOCAINE USP 15% / PHENYLEPHRINE HCL USP 0.25% / PRILOCAINE USP 5%.